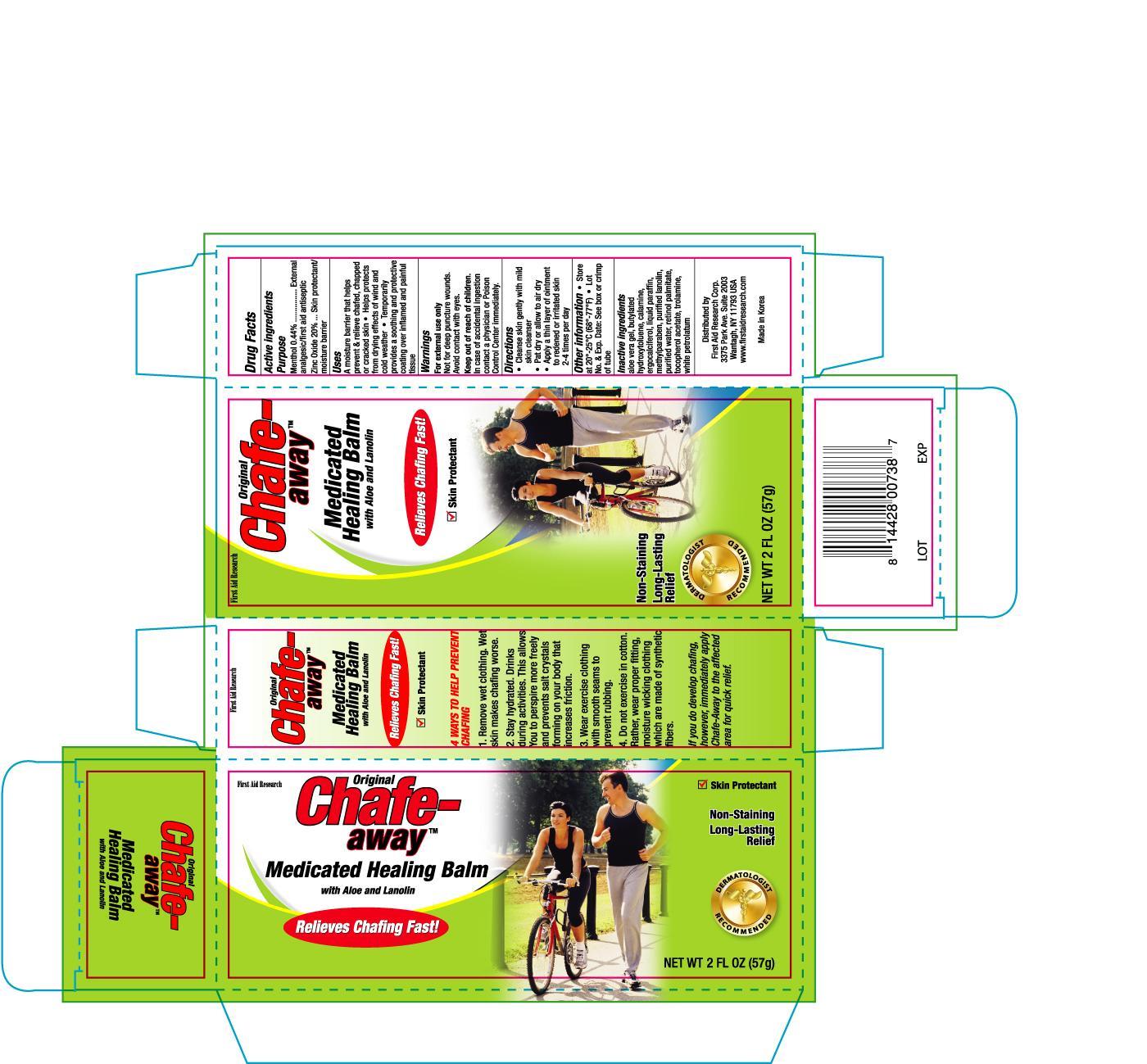 DRUG LABEL: FIRST AID RESEARCH CHAFE AWAY MEDICATED HEALING
NDC: 75983-738 | Form: OINTMENT
Manufacturer: FIRST AID RESEARCH CORP.
Category: otc | Type: HUMAN OTC DRUG LABEL
Date: 20130101

ACTIVE INGREDIENTS: MENTHOL 0.44 g/100 g; ZINC OXIDE 20 g/100 g
INACTIVE INGREDIENTS: ALOE VERA LEAF; BUTYLATED HYDROXYTOLUENE; ERGOCALCIFEROL; MINERAL OIL; METHYLPARABEN; LANOLIN; WATER; TROLAMINE

Drug Facts

Active ingredients Purpose

Menthol 0.44% .......................................................................External analgesic, first aid antiseptic

Zinc Oxide 20% .....................................................................Skin protectant/moisture barrier

Uses

- A moisture barrier that helps prevent and relieve chafed, chapped or cracked skin
- Helps protects from drying effects of wind and cold weather
- Temporarily provides a soothing and protective coating over inflamed and painful tissue

Warning

For external use only

Not for deep or puncture wounds, avoid contact with eyes

Keep out of reach of children.

In case of accidental ingestion contact a physician or Poison Control Center immediately.

Directions

- cleanse skin gently with mild skin cleanser
- pat dry or allow to air dry
- apply a thin layer of ointment to redened or irritated skin 2-4 times per day

Other information

- Store at 20o to 25oC (68o to 77oF)
- Lot No. and Exp. Date: see box or see crimp of tube

Inactive ingredients

Aloe Vera Gel, Butylated Hydroxytoluene, Calamine, Ergocalciferol, Liquid Paraffin, Methylparaben, Purified Lanolin, Purified Water, Retinol Palmitate, Tocopherol Acetate, Trolamine, White Petrolatum

DOSAGE AND ADMINISTRATION

Distributed by:

First Aid Research Corp.

3375 Park Ave. Suite 2003

Wantagh, NY 11793 USA

www.firstaidresearch.com

Made in Korea